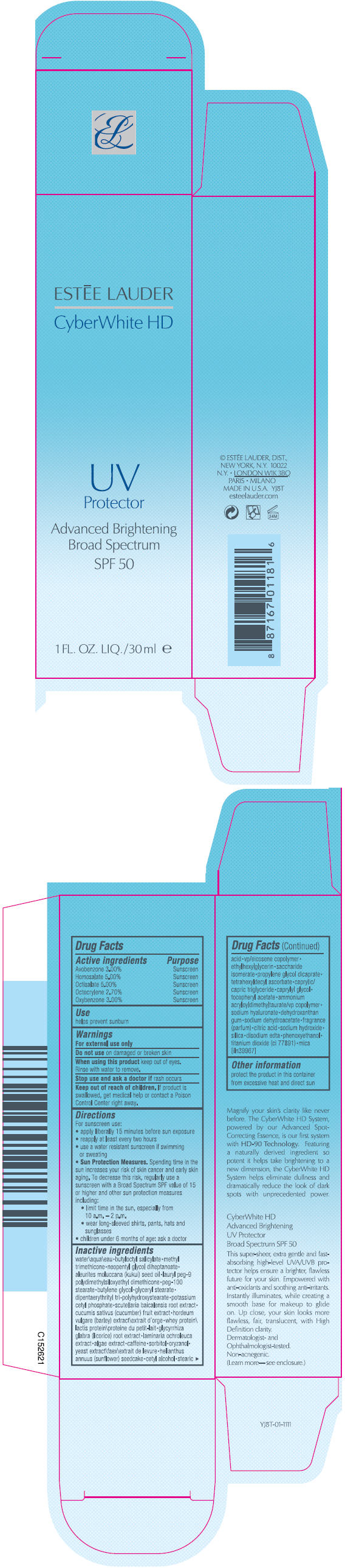 DRUG LABEL: CYBERWHITE HD UV PROTECTOR BROAD SPECTRUM SPF 50
NDC: 11559-037 | Form: LOTION
Manufacturer: ESTEE LAUDER INC
Category: otc | Type: HUMAN OTC DRUG LABEL
Date: 20131029

ACTIVE INGREDIENTS: Avobenzone 0.0309 g/100 mL; Homosalate 0.0515 g/100 mL; Octisalate 0.0515 g/100 mL; Octocrylene 0.0278 g/100 mL; Oxybenzone 0.0309 g/100 mL
INACTIVE INGREDIENTS: water; butyloctyl salicylate; methyl trimethicone; neopentyl glycol diheptanoate; kukui nut oil; lauryl peg-9 polydimethylsiloxyethyl dimethicone; peg-100 stearate; butylene glycol; glyceryl monostearate; potassium cetyl phosphate; scutellaria baicalensis root; cucumber; whey; glycyrrhiza glabra; laminaria ochroleuca; caffeine; sorbitol; gamma oryzanol; yeast; helianthus annuus seedcake; cetyl alcohol; stearic acid; ethylhexylglycerin; saccharide isomerate; propylene glycol dicaprate; tetrahexyldecyl ascorbate; medium-chain triglycerides; caprylyl glycol; .alpha.-tocopherol acetate; ammonium acryloyldimethyltaurate/vp copolymer; hyaluronate sodium; sodium dehydroacetate; citric acid monohydrate; sodium hydroxide; silicon dioxide; edetate disodium; phenoxyethanol; titanium dioxide; mica

CYBERWHITE HD UV PROTECTOR BROAD SPECTRUM SPF 50

Drug Facts

ACTIVE INGREDIENT

Active ingredients | Purpose
Avobenzone 3.00% | Sunscreen
Homosalate 5.00% | Sunscreen
Octisalate 5.00% | Sunscreen
Octocrylene 2.70% | Sunscreen
Oxybenzone 3.00% | Sunscreen

Use

helps prevent sunburn

Warnings

For external use only

Do not use on damaged or broken skin

When using this product keep out of eyes.

Rinse with water to remove.

Stop use and ask a doctor if rash occurs

Keep out of reach of children. If product is swallowed, get medical help or contact a Poison Control Center right away.

Directions

For sunscreen use:

- apply liberally 15 minutes before sun exposure
- reapply at least every two hours
- use a water resistant sunscreen if swimming or sweating
- Sun Protection Measures. Spending time in the sun increases your risk of skin cancer and early skin aging. To decrease this risk, regularly use a sunscreen with a Broad Spectrum SPF value of 15 or higher and other sun protection measures including:
  - limit time in the sun, especially from 10 a.m. – 2 p.m.
  - wear long-sleeved shirts, pants, hats and sunglasses
- children under 6 months of age: ask a doctor

Inactive ingredients

water\aqua\eau • butyloctyl salicylate • methyl trimethicone • neopentyl glycol diheptanoate • aleurites moluccana (kukui) seed oil • lauryl peg-9 polydimethylsiloxyethyl dimethicone • peg-100 stearate • butylene glycol • glyceryl stearate • dipentaerythrityl tri-polyhydroxystearate • potassium cetyl phosphate • scutellaria baicalensis root extract • cucumis sativus (cucumber) fruit extract • hordeum vulgare (barley) extract\extrait d'orge • whey protein\lactis protein\proteine du petit-lait • glycyrrhiza glabra (licorice) root extract • laminaria ochroleuca extract • algae extract • caffeine • sorbitol • oryzanol • yeast extract\faex\extrait de levure • helianthus annuus (sunflower) seedcake • cetyl alcohol • stearic acid • vp/eicosene copolymer • ethylhexylglycerin • saccharide isomerate • propylene glycol dicaprate • tetrahexyldecyl ascorbate • caprylic/capric triglyceride • caprylyl glycol • tocopheryl acetate • ammonium acryloyldimethyltaurate/vp copolymer • sodium hyaluronate • dehydroxanthan gum • sodium dehydroacetate • fragrance (parfum) • citric acid • sodium hydroxide • silica • disodium edta • phenoxyethanol • titanium dioxide (ci 77891) • mica [iln39967]

Other information

protect the product in this container from excessive heat and direct sun

PRINCIPAL DISPLAY PANEL - 30ml Bottle Carton

ESTĒE LAUDER

CyberWhite HD

UV
Protector

Advanced Brightening
Broad Spectrum
SPF 50

1 FL. OZ. LIQ./30ml e